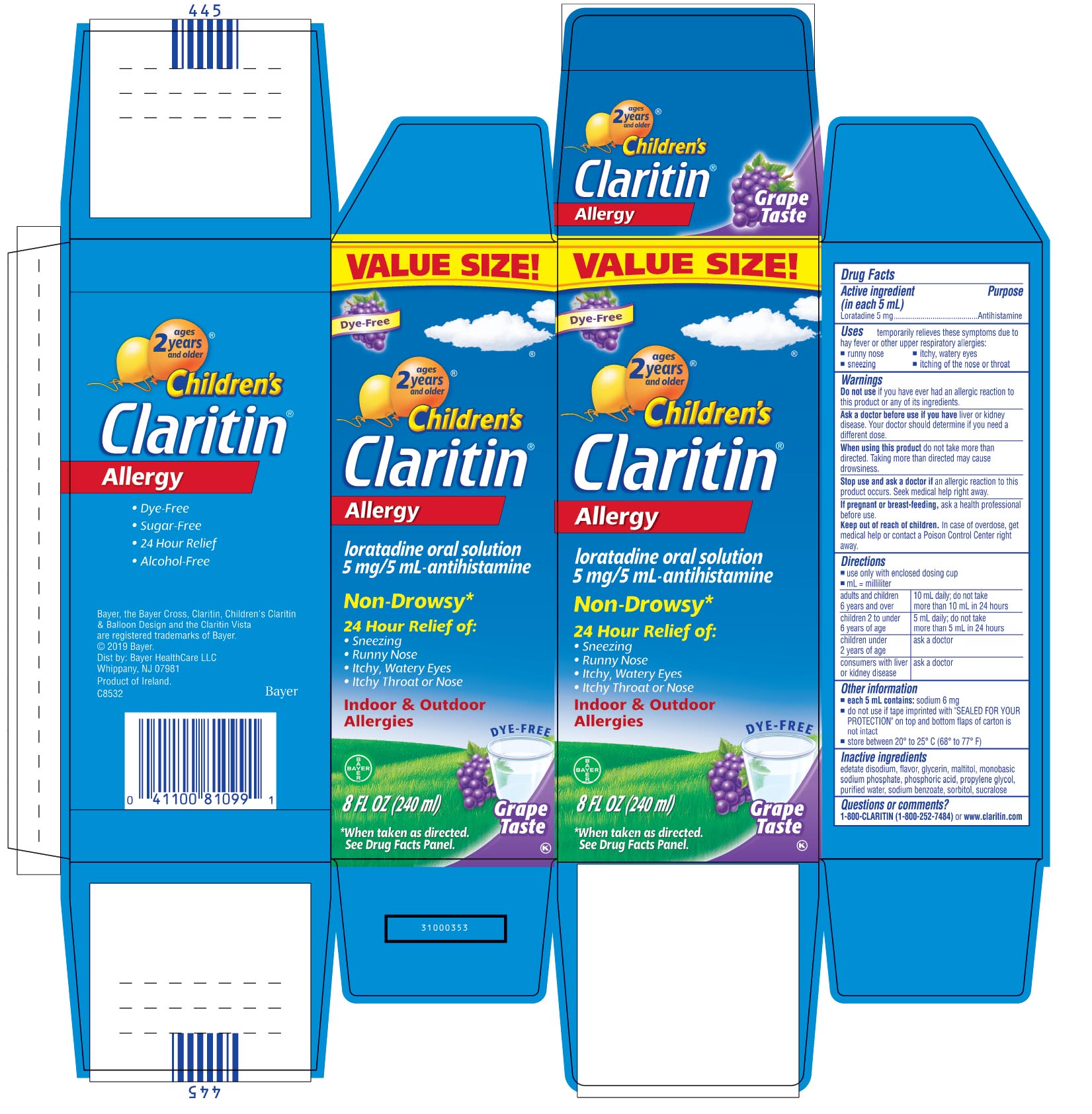 DRUG LABEL: Children Claritin
NDC: 11523-4360 | Form: SOLUTION
Manufacturer: Bayer HealthCare LLC.
Category: otc | Type: HUMAN OTC DRUG LABEL
Date: 20250515

ACTIVE INGREDIENTS: LORATADINE 5 mg/5 mL
INACTIVE INGREDIENTS: SORBITOL; EDETATE DISODIUM; MALTITOL; GLYCERIN; PHOSPHORIC ACID; SUCRALOSE; WATER; SODIUM PHOSPHATE, MONOBASIC; PROPYLENE GLYCOL; SODIUM BENZOATE

Children's Claritin Allergy (Grape Flavor)

Active ingredient (in each 5 mL teaspoonful)

Loratadine 5 mg

Purpose

Antihistamine

Uses

temporarily relieves these symptoms due to hay fever or other upper respiratory allergies:

- runny nose
- sneezing
- itchy, watery eyes
- itching of the nose or throat

Do not use if you have ever had an allergic reaction to this product or any of its ingredients.

Ask a doctor before use if you have liver or kidney disease. Your doctor should determine if you need a different dose.

When using this product do not take more than directed. Taking more than directed may cause drowsiness.

Stop use and ask a doctor if an allergic reaction to this product occurs. Seek medical help right away.

PREGNANCY OR BREAST FEEDING

If pregnant or breast-feeding, ask a health professional before use.

Keep out of reach of children. In case of overdose, get medical help or contact a Poison Control Center right away.

Directions

Use only with enclosed dosing cup

- adults and children 6 years and over: 10 mL daily; do not take more than 10 mL in 24 hours
- children 2 to under 6 years of age: 5 mL daily; do not take more than 5 mL in 24 hours
- children under 2 years of age: ask a doctor
- consumers with liver or kidney disease: ask a doctor

OTHER SAFETY INFORMATION

- each 5 mL contains: sodium 6 mg
- do not use if tape imprinted with “SEALED FOR YOUR PROTECTION” on top and bottom flaps of carton is not intact.
- store between 20° and 25°C (68° and 77°F)

INACTIVE INGREDIENT

edetate disodium, flavor, glycerin, maltitol, monobasic sodium phosphate, phosphoric acid, propylene glycol, purified water, sodium benzoate, sorbitol, sucralose

Questions or comments?

1-800-CLARITIN (1-800-252-7484) or www.claritin.com